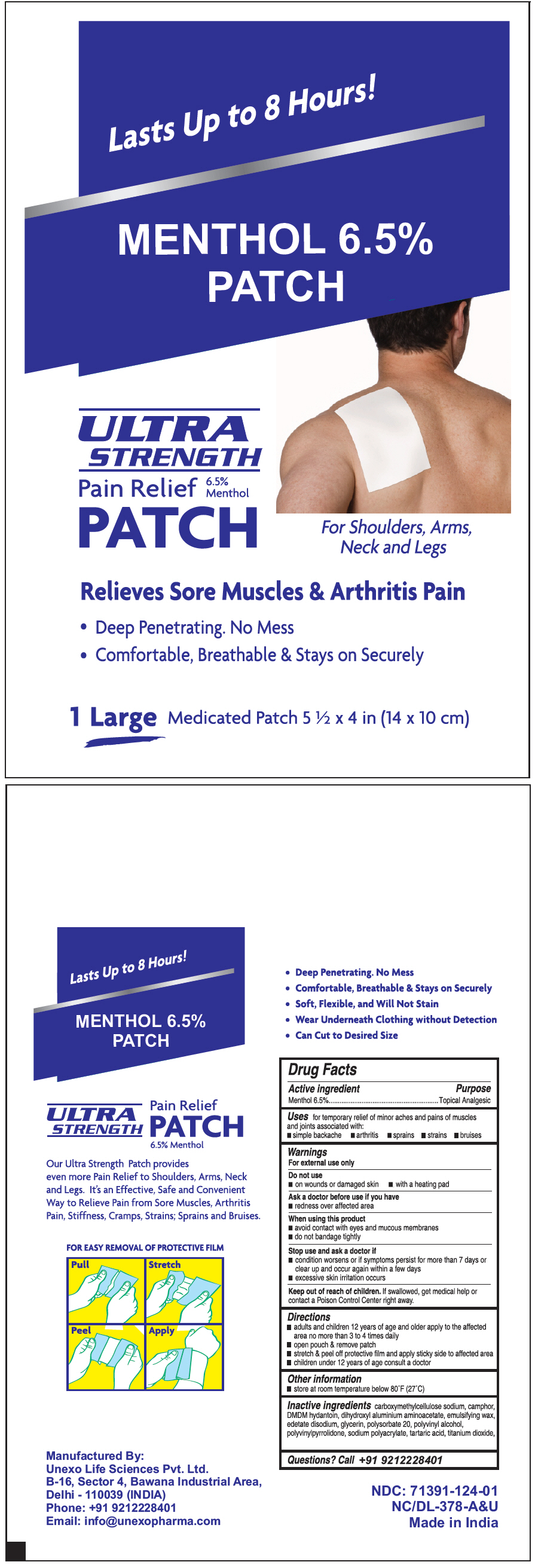 DRUG LABEL: Menthol 6.5%
NDC: 71391-124 | Form: PATCH
Manufacturer: Unexo Life Sciences, Private Limited
Category: otc | Type: HUMAN OTC DRUG LABEL
Date: 20250110

ACTIVE INGREDIENTS: menthol, unspecified form 910 mg/1 1
INACTIVE INGREDIENTS: CARBOXYMETHYLCELLULOSE; CAMPHOR (SYNTHETIC); DMDM hydantoin; DIHYDROXYALUMINUM AMINOACETATE; WHITE WAX; Edetate Sodium; Glycerin; Polysorbate 20; Polyvinyl Alcohol, Unspecified; POVIDONE K60; SODIUM POLYACRYLATE (8000 MW); Tartaric acid; Titanium dioxide

Menthol 6.5% Patch

Drug Facts

Active Ingredient

PURPOSE

Menthol 6.5% - Topical Analgesic

Uses

For temporary relief of minor aches and pains of muscles and joints associated with:

- Simple backache
- Arthritis
- Sprains
- Strains
- Bruises

Warnings

For external use only

Do not use

- On wounds or damaged skin
- With a heating pad

Ask a doctor before use if you have

- Redness over affected area

When using this product

- Avoid contact with eyes and mucous membranes
- Do not bandage tightly

Stop use and ask a doctor if

- Condition worsens or if symptoms persist for more than 7 days or clear up and occur again within a few days
- Excessive skin irritation occurs

Keep out of reach of children. If swallowed, get medical help or contact a Poison Control Center right away.

Directions

- Adults and children 12 years of age and older apply to the affected area no more than 3 to 4 times daily
- Open pouch & remove patch
- Peel off protective film and apply sticky side to affected area
- Children under 12 years of age consult a doctor

Other Information

- Store at room temperature below 80°F (27°C)

Inactive Ingredients

carboxymethylcellulose sodium, camphor, DMDM hydantoin, dihydroxyl aluminium aminoacetate, emulsifying wax, edetate disodium, glycerin, polysorbate 20, polyvinyl alcohol, polyvinylpyrrolidone, sodium polyacrylate, tartaric acid, titanium dioxide, water

Questions

Call +91 9212228401

Manufactured By:
UNEXO LIFE SCIENCES PVT. LTD.
B-16. Sector 4, Bawana Industrial Area,
Delhi – 110039 (INDIA)

PRINCIPAL DISPLAY PANEL - 1 Patch Pouch

Lasts Up to 8 Hours!

MENTHOL 6.5%
PATCH

ULTRA
STRENGTH

Pain Relief
PATCH
6.5%
Menthol

For Shoulders, Arms,
Neck and Legs

Relieves Sore Muscles & Arthritis Pain

- Deep Penetrating. No Mess
- Comfortable, Breathable & Stays on Securely

1 Large Medicated Patch 5 ½ x 4 in (14 x 10 cm)